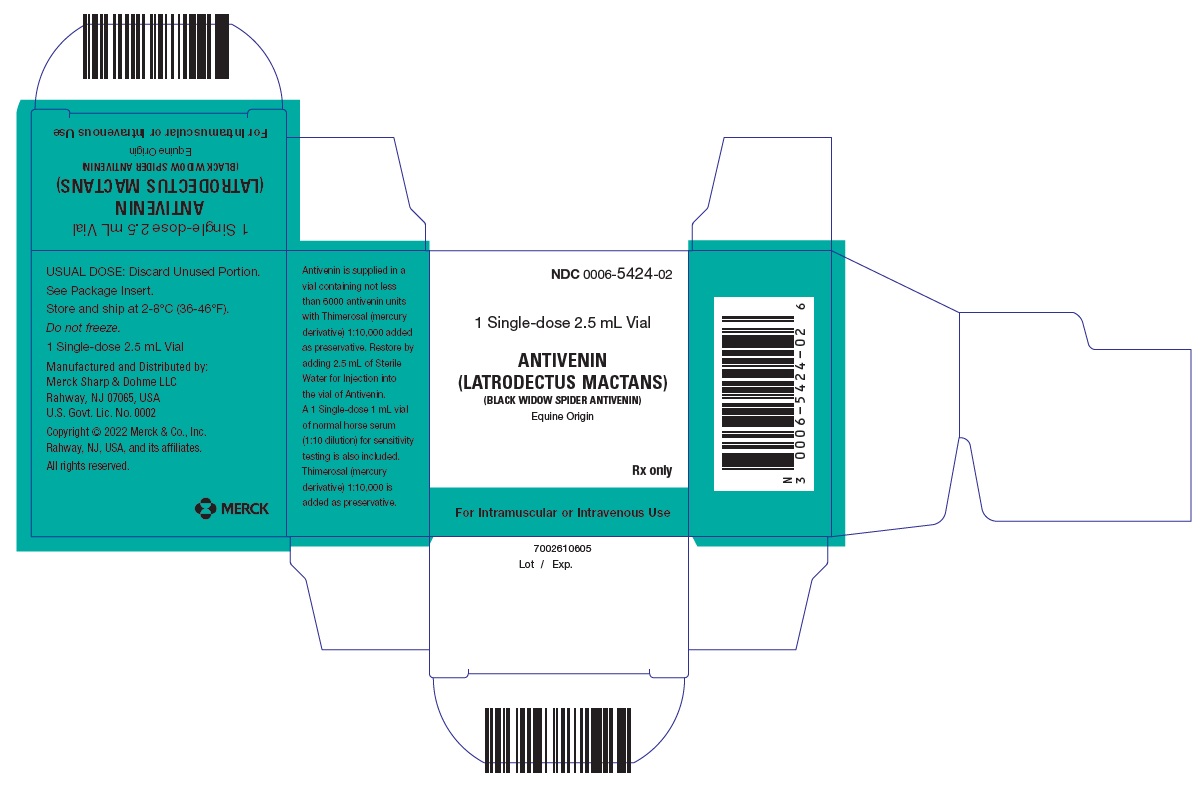 DRUG LABEL: ANTIVENIN
NDC: 0006-5424 | Form: KIT | Route: INTRAMUSCULAR
Manufacturer: Merck Sharp & Dohme LLC
Category: other | Type: PLASMA DERIVATIVE
Date: 20241008

ACTIVE INGREDIENTS: BLACK WIDOW SPIDER (LATRODECTUS MACTANS) IMMUNE GLOBULIN ANTIVENIN (EQUINE) 6000 [iU]/2.5 mL
INACTIVE INGREDIENTS: THIMEROSAL; SERUM, HORSE; THIMEROSAL

ANTIVENIN
(LATRODECTUS MACTANS)
(Black Widow Spider Antivenin)
Equine Origin

DESCRIPTION

Antivenin (Latrodectus mactans) is a sterile, non-pyrogenic preparation derived by drying a frozen solution of specific venom-neutralizing globulins obtained from the blood serum of healthy horses immunized against venom of black widow spiders (Latrodectus mactans). It is standardized by biological assay on mice, in terms of one dose of Antivenin neutralizing the venom in not less than 6000 mouse LD50 of Latrodectus mactans. Thimerosal (mercury derivative) 1:10,000 is added as a preservative. When constituted as specified, it is opalescent, ranging in color from light (straw) to very dark (iced tea), and contains not more than 20.0 percent of solids.

Each single-dose vial contains not less than 6000 Antivenin units. One unit of Antivenin will neutralize one average mouse lethal dose of black widow spider venom when the Antivenin and the venom are injected simultaneously in mice under suitable conditions.

CLINICAL PHARMACOLOGY

The pharmacological mode of action is unknown and metabolic and pharmacokinetic data in humans are unavailable.

INDICATIONS AND USAGE

Antivenin (Latrodectus mactans) is used to treat patients with symptoms due to bites by the black widow spider (Latrodectus mactans). Early use of the Antivenin is emphasized for prompt relief.

Local muscular cramps begin from 15 minutes to several hours after the bite which usually produces a sharp pain similar to that caused by puncture with a needle. The exact sequence of symptoms depends somewhat on the location of the bite. The venom acts on the myoneural junctions or on the nerve endings, causing an ascending motor paralysis or destruction of the peripheral nerve endings. The groups of muscles most frequently affected at first are those of the thigh, shoulder, and back. After a varying length of time, the pain becomes more severe, spreading to the abdomen, and weakness and tremor usually develop. The abdominal muscles assume a boardlike rigidity, but tenderness is slight. Respiration is thoracic. The patient is restless and anxious. Feeble pulse, cold, clammy skin, labored breathing and speech, light stupor, and delirium may occur. Convulsions also may occur, particularly in small children. The temperature may be normal or slightly elevated. Urinary retention, shock, cyanosis, nausea and vomiting, insomnia, and cold sweats also have been reported. The syndrome following the bite of the black widow spider may be confused easily with any medical or surgical condition with acute abdominal symptoms.

The symptoms of black widow spider bite increase in severity for several hours, perhaps a day, and then very slowly become less severe, gradually passing off in the course of two or three days except in fatal cases. Residual symptoms such as general weakness, tingling, nervousness, and transient muscle spasm may persist for weeks or months after recovery from the acute stage.

If possible, the patient should be hospitalized. Other additional measures giving greatest relief are prolonged warm baths and intravenous injection of 10 mL of 10 percent solution of calcium gluconate repeated as necessary to control muscle pain. Morphine also may be required to control pain. Barbiturates may be used for extreme restlessness. However, as the venom is a neurotoxin, it can cause respiratory paralysis. This must be borne in mind when considering use of morphine or a barbiturate. Adrenocorticosteroids have been used with varying degrees of success. Supportive therapy is indicated by the condition of the patient. Local treatment of the site of the bite is of no value. Nothing is gained by applying a tourniquet or by attempting to remove venom from the site of the bite by incision and suction.

In otherwise healthy individuals between the ages of 16 and 60, the use of Antivenin may be deferred and treatment with muscle relaxants may be considered.

WARNINGS

Prior to treatment with any product prepared from horse serum, a careful review of the patient's history should be taken emphasizing prior exposure to horse serum or any allergies. Serum sickness and even death could result from the use of horse serum in a sensitive patient. A skin or conjunctival test should be performed prior to administration of Antivenin. However, an anaphylactic reaction to Antivenin may occur even following a negative skin or conjunctival test (see ADVERSE REACTIONS).

Skin test: Inject into (not under) the skin not more than 0.02 mL of the test material (1:10 dilution of normal horse serum in physiologic saline). Evaluate result in 10 minutes. A positive reaction is an urticarial wheal surrounded by a zone of erythema. A control test using Sodium Chloride Injection facilitates interpretation of the results.

Conjunctival test: For adults instill into the conjunctival sac one drop of a 1:10 dilution of horse serum and for children one drop of 1:100 dilution. Itching of the eye and reddening of the conjunctiva indicate a positive reaction, usually within 10 minutes.

Patients should be observed for serum sickness for an average of 8 to 12 days following administration of Antivenin.

Desensitization should be attempted only when the administration of Antivenin is considered necessary to save life. Epinephrine must be available in case of untoward reaction.

Desensitization: If the history is positive or the results of the sensitivity tests are mildly or questionably positive, Antivenin should be administered as follows to reduce the risk of an immediate severe allergic reaction:

1. In separate sterile vials or syringes prepare 1:10 or 1:100 dilutions of Antivenin in Sodium Chloride for Injection.
2. Allow at least 15 but preferably 30 minutes between injections and only proceed with the next dose if no reactions occurred following the previous dose.
3. Using a tuberculin syringe, inject subcutaneously 0.1, 0.2 and 0.5 mL of the 1:100 dilution at 15 or 30 minute intervals; repeat with the 1:10 dilution, and finally the undiluted Antivenin.
4. If there is a reaction after any of the injections, place a tourniquet proximal to the sites of injection and administer epinephrine, 1:1000 (0.3 to 1.0 mL subcutaneously, 0.05 to 0.1 mL intravenously), proximal to the tourniquet or into another extremity. Wait at least 30 minutes before giving another injection of Antivenin, the amount of which should be the same as the last one not evoking a reaction.
5. If no reaction has occurred after 0.5 mL of undiluted Antivenin has been given, it is probably safe to continue the dose at 15 minute intervals until the entire dose has been injected.

PRECAUTIONS

Patients with Asthma

Anaphylactic reactions and death have been reported in patients with a medical history of asthma.

Carcinogenesis, Mutagenesis, Impairment of Fertility

No long term studies in animals have been performed to evaluate the potential for carcinogenesis, mutagenesis, or impairment of fertility.

Pregnancy

Animal reproduction studies have not been conducted with Black Widow Spider Antivenin. It is also not known whether Black Widow Spider Antivenin can cause fetal harm when administered to a pregnant woman or can affect reproduction capacity. Black Widow Spider Antivenin should be given to a pregnant woman only if clearly needed.

Nursing Mothers

It is not known whether this drug is excreted in human milk. Because many drugs are excreted in human milk, caution should be exercised when Black Widow Spider Antivenin is administered to a nursing woman.

Pediatric Use

Controlled clinical studies for safety and effectiveness in children have not been conducted.

Geriatric Use

Reported clinical experience has not identified differences in responses between the elderly and younger patients. Because of the increased risk of complications from envenomation in elderly patients, the standard of care described in the literature suggests that patients older than 60 years of age should be given Antivenin as a preferred initial therapy (see INDICATIONS AND USAGE).

ADVERSE REACTIONS

The following adverse reactions have been reported following the use of Antivenin: Hypersensitivity reactions including anaphylaxis and serum sickness. Muscle cramps have also been reported.

DOSAGE AND ADMINISTRATION

Using a sterile syringe, inject 2.5 mL of Sterile Water for Injection into the single-dose vial of Antivenin. With the needle still in the rubber stopper, shake the vial to dissolve the contents completely.

Parenteral drug products should be inspected visually for particulate matter prior to administration, whenever solution and container permit (see DESCRIPTION).

The dose for adults and children is the entire contents of a restored single-dose vial (2.5 mL) of Antivenin. It may be given intramuscularly, preferably in the region of the anterolateral thigh so that a tourniquet may be applied in the event of a systemic reaction. Symptoms usually subside in 1 to 3 hours. Although one dose of Antivenin usually is adequate, a second dose may be necessary in some cases. Discard unused portion.

Antivenin also may be given intravenously in 10 to 50 mL of saline solution over a 15 minute period. It is the preferred route in severe cases, or when the patient is under 12, or in shock. One restored single-dose vial usually is enough. Discard unused portion.

HOW SUPPLIED

No. 5424 — Antivenin (Latrodectus mactans), equine origin is a white to gray crystalline powder, each single-dose vial containing not less than 6000 Antivenin units. Thimerosal (mercury derivative) 1:10,000 is added as preservative, NDC 0006-5424-02. A single-dose 1 mL vial of normal horse serum (1:10 dilution) for sensitivity testing is also included. Thimerosal (mercury derivative) 1:10,000 is added as preservative.

Storage

Antivenin must be stored and shipped at 2-8°C (36-46°F). When reconstituted as directed, the color of Antivenin ranges from light (straw) to very dark (iced tea), but the color has no effect on potency. Do not freeze.

REFERENCES

Barron, W. E.: Spider Bites, J. Med. Ass. Georgia 49: 511-512, Oct. 1960.

Micks, D. W.: Insects and Other Arthropods of Medical Importance in Texas, Tex. Rep. Biol. & Med. 18: 624-635, Winter 1960.

Prince, G. E.: Arachnidism in Children, J. Pediat. 49: 101-108, July 1956.

Russell, F. E.: Injuries by Venomous Animals in the United States, J. Amer. Med. Ass. 177: 903-907, Sept. 30, 1961.

Russell, F. E.: Muscle Relaxants in Black Widow Spider (Latrodectus mactans) Poisoning, Amer. J. Med. Sci. 243: 159-162, Feb. 1962.

Russell, F. E.: Venom Poisoning, Rational Drug Therap. 5: 5-6, Aug. 1971.

Distributed by: Merck Sharp & Dohme LLC
Rahway, NJ 07065, USA

For patent information: www.msd.com/research/patent

Copyright © 2013-2023 Merck & Co., Inc., Rahway, NJ, USA, and its affiliates.
All rights reserved.

Revised: 04/2023

uspi-mk9001-i-2304r024

This is a representative sample of the packaging. Please see How Supplied section for a complete list of available packaging. PRINCIPAL DISPLAY PANEL - Kit Carton

NDC 0006-5424-02

1 Single-dose 2.5 mL Vial

ANTIVENIN
(LATRODECTUS MACTANS)
(BLACK WIDOW SPIDER ANTIVENIN)
Equine Origin

Rx only

For Intramuscular or Intravenous Use